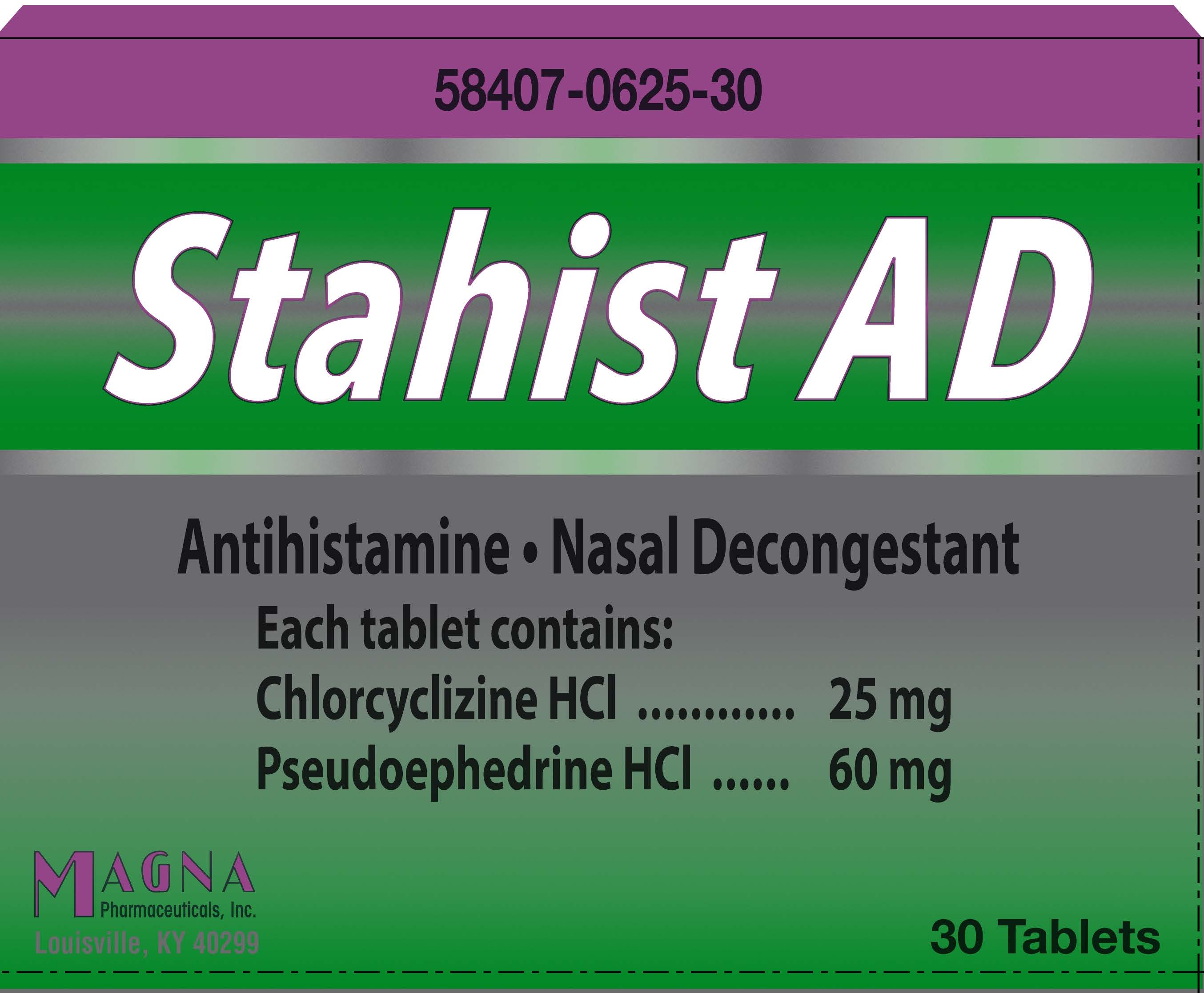 DRUG LABEL: STAHIST AD
NDC: 58407-625 | Form: TABLET
Manufacturer: Magna Pharmaceuticals, Inc.
Category: otc | Type: HUMAN OTC DRUG LABEL
Date: 20251003

ACTIVE INGREDIENTS: CHLORCYCLIZINE HYDROCHLORIDE 25 mg/1 1; PSEUDOEPHEDRINE HYDROCHLORIDE 60 mg/1 1
INACTIVE INGREDIENTS: MICROCRYSTALLINE CELLULOSE; MAGNESIUM STEARATE; SODIUM STARCH GLYCOLATE TYPE A POTATO

Stahist AD

Drug Facts

ACTIVE INGREDIENT

Active Ingredients (in each immediate-release tablet) | Purpose
Chlorcyclizine HCl 25 mg | Antihistamine
Pseudoephedrine HCl 60 mg | Nasal Decongestant

Uses

temporarily relieves these symptoms due to the common cold, hay fever (allergic rhinitis) or other upper respiratory allergies:

- runny nose
- sneezing
- itching of the nose or throat
- itchy, watery eyes
- nasal congestion
- reduces swelling of nasal passages

Warnings

Do not exceed recommended dosage.

Do not use this product

- If you are taking a prescription monoamine oxidase inhibitor (MAOI) (certain drugs for depression, psychiatric, or emotional conditions, or Parkinson's disease), or for two weeks after stopping the MAOI drug. If you do not know if your prescription drug contains MAOI, ask a doctor or pharmacist before taking this product.

Ask a doctor before use if you have

- a breathing problem such as emphysema or chronic bronchitis
- glaucoma
- heart disease
- high blood pressure
- thyroid disease
- diabetes melitus
- difficulty in urination due to enlargement of the prostate gland

Ask a doctor before use if you are taking sedatives or tranquilizers

When using this product

- excitability may occur, especially in children
- may cause drowsiness
- alcohol, sedatives and tranquilizers may increase drowsiness effect
- avoid alcoholic beverages
- use caution when driving a motor vehicle or operating machinery

Stop use and ask a doctor if

- nervousness, dizziness or sleeplessness occur
- symptoms do not improve within 7 days or are accompanied by fever
- new symptoms occur

PREGNANCY OR BREAST FEEDING

If pregnant or breast-feeding,ask a health professional before use.

Keep out of reach of children.

In case of accidental overdose, seek professional help or contact a Poison Control Center immediately.

Directions

Do not exceed recommended dosage.

Adults and children 12 years of age and over: | 1 tablet by mouth every 6-8 hours, not to exceed 3 tablets in 24 hours, or as directed by a doctor
Children 6 to under 12 years of age: | ½ tablet by mouth every 6-8 hours, not to exceed 1½ tablets in 24 hours, or as directed by a doctor
Children under 6 years of age | Consult a doctor

Inactive ingredients

Magnesium Stearate, Microcrystalline Cellulose, Sodium Starch Glycolate

Questions or Comments?

Call 1-888-206-5525 • www.magnaweb.com

Rev. 10/11

PACKAGE LABEL

Add image transcription here...